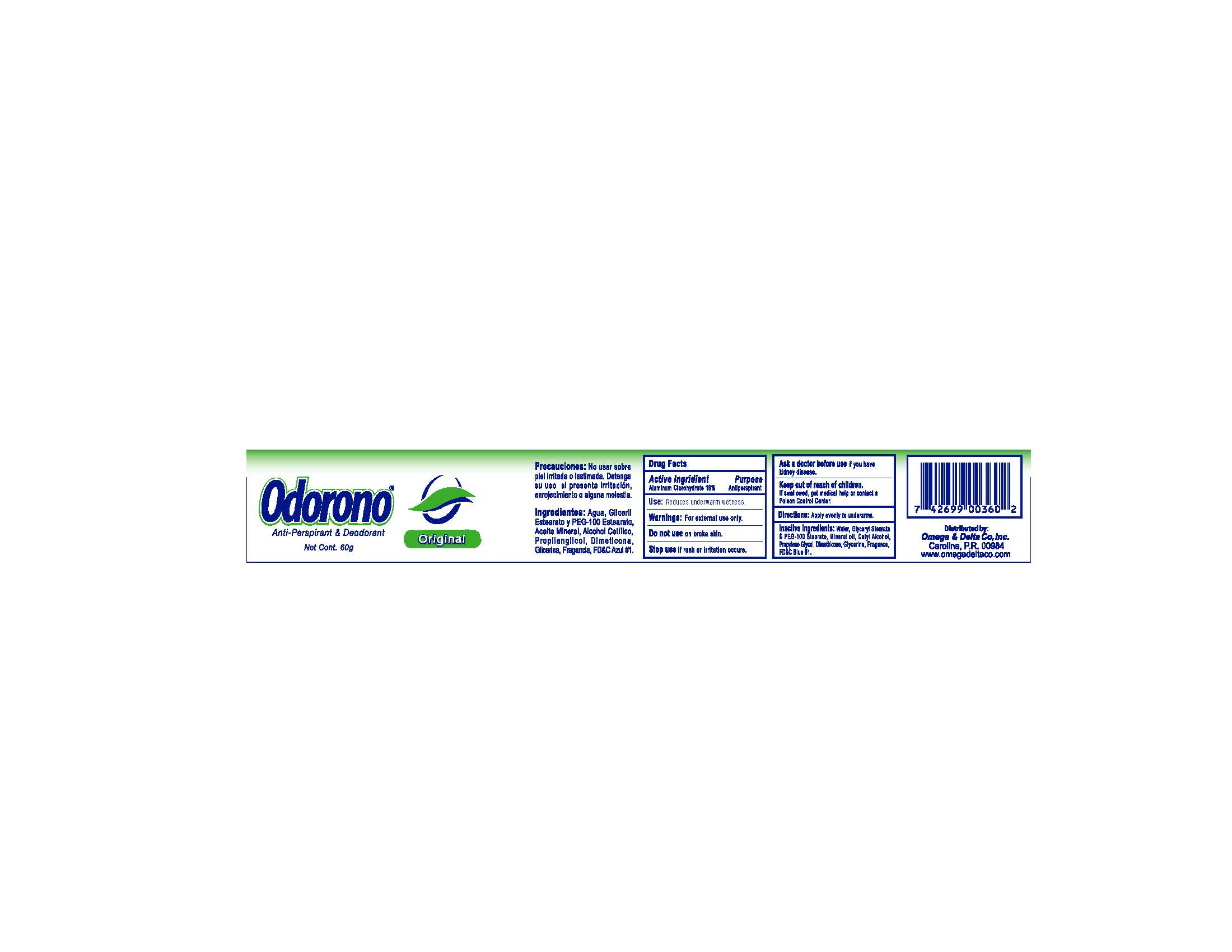 DRUG LABEL: Odorono
NDC: 51048-360 | Form: CREAM
Manufacturer: Omega & Delta Co
Category: otc | Type: HUMAN OTC DRUG LABEL
Date: 20250827

ACTIVE INGREDIENTS: ALUMINUM CHLOROHYDRATE 16 g/100 g
INACTIVE INGREDIENTS: WATER; GLYCERYL STEARATE/PEG-100 STEARATE; MINERAL OIL; CETYL ALCOHOL; PROPYLENE GLYCOL; DIMETHICONE; GLYCERIN

Odorono Antiperspirant Deodorant Cream

Drug Facts

Active Ingredients

Aluminum Chlorohydrate 16%

Purpose

Antiperspirant

INDICATIONS AND USAGE

Use: Reduces underarm wetness

Warnings: For external use only

Do not use on broken skin

Stop use if rash or irritation occurs

Ask a doctor before use if you have kidney disease

Keep out of reach of children. If swallowed, get medical help or contact a Poison Control Center.

DOSAGE AND ADMINISTRATION

Directions: Apply evenly to underarms only

INACTIVE INGREDIENT

Inactive Ingredients: Water, Glyceryl Stearate & PEG-100 Stearate, Mineraol Oil, Cetyl Alcohol, Propylene Glycol, Dimethicone, Glycerine, Fragrance, FD&C Blue #1.

Distributed by:

Omega & Delta Co., Inc.

Carolina, P.R. 00984

www.omegadeltaco.com